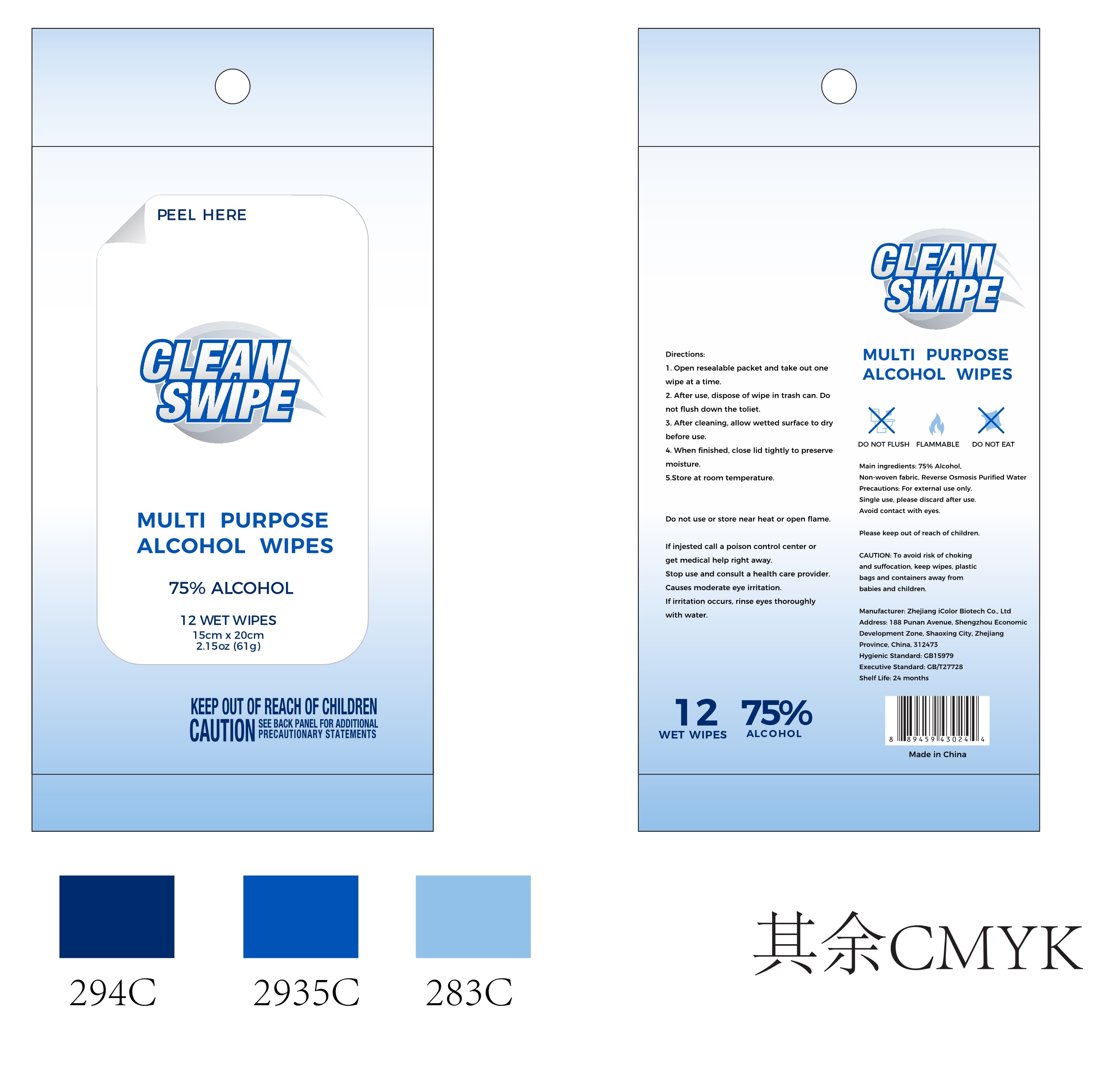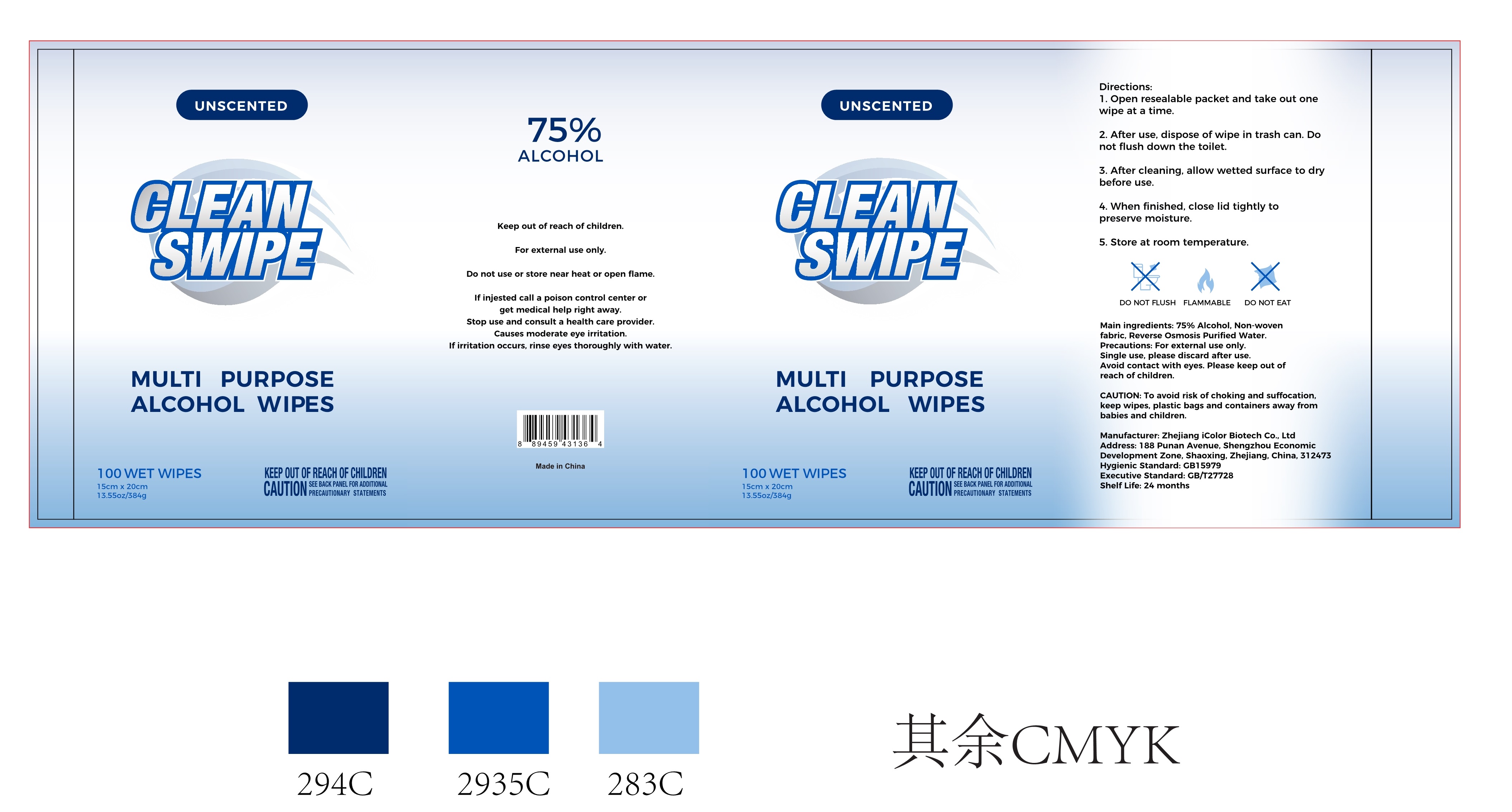 DRUG LABEL: CLEAN SWIPE
NDC: 74934-045 | Form: CLOTH
Manufacturer: Zhejiang iColor Biotech Co., Ltd
Category: otc | Type: HUMAN OTC DRUG LABEL
Date: 20200801

ACTIVE INGREDIENTS: ALCOHOL 75 mL/100 1
INACTIVE INGREDIENTS: WATER

74934-045 CLEAN SWIPE

Active Ingredient(s)

75% Alcohol

Purpose

/

Use

For external use only.
Single use, please discard after use
Avoid contact with eyes

Warnings

To avoid risk of chokingand suffocation, keep wipes, plasticbags and containers away frombabies and children

Do not use or store near heat or open flame.
If injested call a poison control center or get medical help right away

WHEN USING

/

Stop use and consult a health care provider.
Causes moderate eye irritationIf irritation occurs, rinse eyes thoroughly with water

Please keep out of reach of children

Directions

1. Open resealable packet and take out one wipe at a time
2. After use, dispose of wipe in trash can Do not flush down the toliet
3. After cleaning, allow wetted surface to dry before use
4. When finished close lid tightly to preserve moisture
5.Store at room temperature.

Other information

/

Inactive ingredients

Non-woven fabric, Reverse Osmosis purified Water